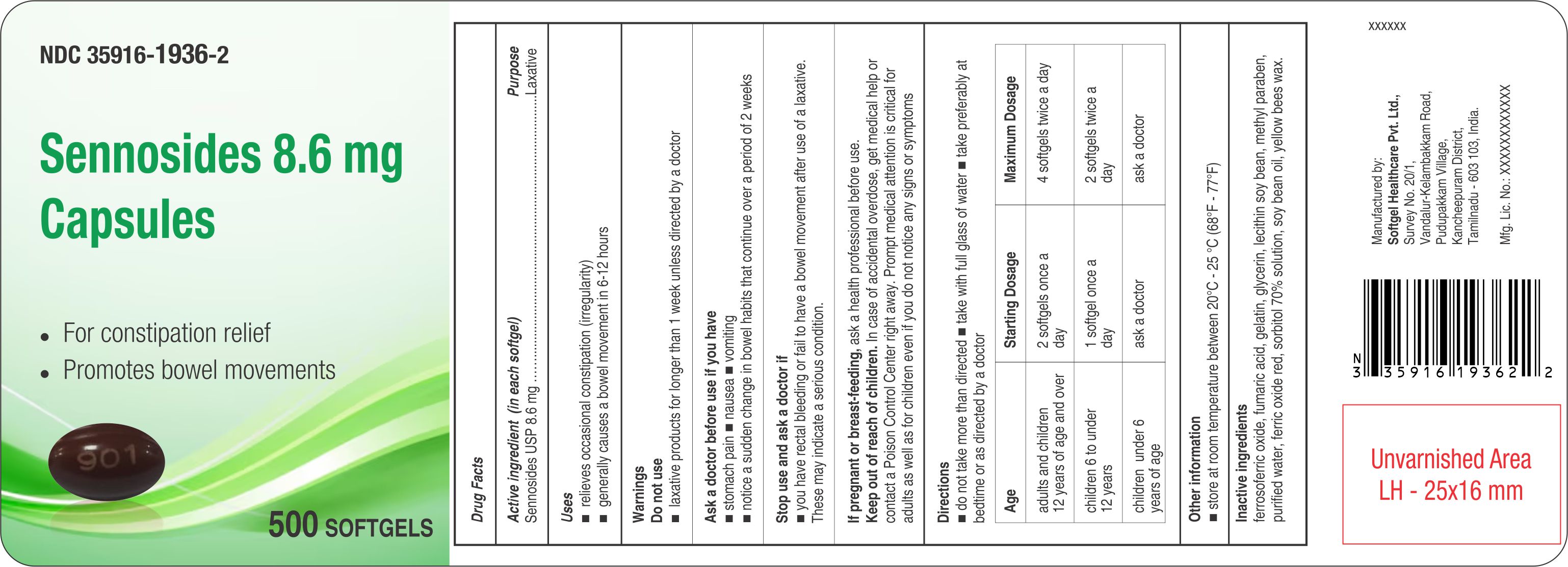 DRUG LABEL: Sennosides
NDC: 35916-1936 | Form: CAPSULE, LIQUID FILLED
Manufacturer: Softgel Healthcare Pvt Ltd
Category: otc | Type: HUMAN OTC DRUG LABEL
Date: 20260127

ACTIVE INGREDIENTS: SENNOSIDES 8.6 mg/1 1
INACTIVE INGREDIENTS: SOYBEAN OIL; GELATIN; FERROSOFERRIC OXIDE; SORBITOL SOLUTION 70%; WATER; GLYCERIN; LECITHIN, SOYBEAN; FERRIC OXIDE RED; METHYLPARABEN; YELLOW WAX; FUMARIC ACID

Sennosides 8.6 mg

Active ingredient (in each softgel)

Sennosides USP 8.6 mg

Purpose

Laxative

Uses

- relieves occasional constipation (irregularity)
- generally causes a bowel movement in 6-12 hours

Warnings Do not use

- laxative products for longer than 1 week unless directed by a doctor

Ask a doctor before use if you have

- stomach pain
- nausea
- vomiting
- notice a sudden change in bowel habits that continue over a period of 2 weeks

Stop use and ask a doctor if

- you have rectal bleeding or fail to have a bowel movement after use of a laxative. These may indicate a serious condition.

If pregnant or breast-feeding,

ask a health professional before use.

Keep out of reach of children.

In case of accidental overdose, get medical help or contact a Poison Control Center right away. Prompt medical attention is critical for adults as well as for children even if you do not notice any signs or symptoms

Directions

- do not take more than directed
- take with full glass of water
- take preferably at bedtime or as directed by a doctor
  Age | Starting Dosage | Maximum Dosage
  adults and children 12 years of age and over | 2 softgels once a day | 4 softgels twice a day
  children 6 to under 12 years | 1 softgel once a day | 2 softgels twice a day
  children under 6 years of age | ask a doctor | ask a doctor

Other information

- store at room temperature between 20°C - 25°C (68°F - 77°F)

Inactive ingredients

ferrosoferric oxide, fumaric acid, gelatin, glycerin, lecithin soybean, methyl paraben, purified water, ferric oxide red, sorbitol 70% solution, soy bean oil, yellow bees wax.